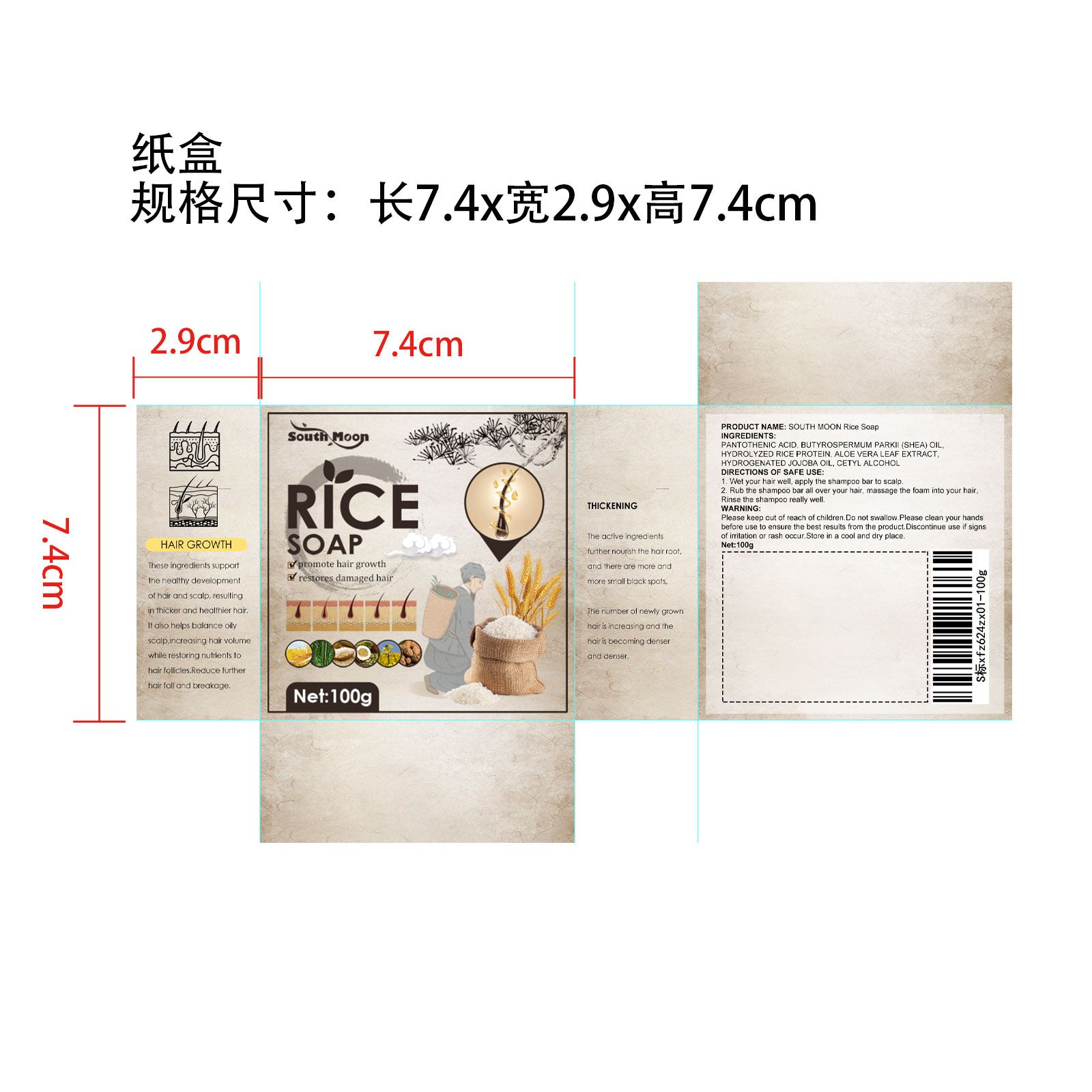 DRUG LABEL: RiceShampooSoap
NDC: 84778-013 | Form: SOAP
Manufacturer: Guangzhou Yixin Cross-border E-commerce Co., Ltd.
Category: otc | Type: HUMAN OTC DRUG LABEL
Date: 20241021

ACTIVE INGREDIENTS: HYDROLYZED RICE PROTEIN (ENZYMATIC; 2000 MW) 6 g/6 g
INACTIVE INGREDIENTS: SODIUM LACTATE; FRAGRANCE 13576; BEHENTRIMONIUM METHOSULFATE; CETYL ALCOHOL; ALOE VERA LEAF; SODIUM COCOYL ISETHIONATE; STEARIC ACID

COMPONENTS

Hydrolyzed Rice Protein 6g

PURPOSE

Anti-hair loss

INDICATIONS AND USAGE

wet hair to be cleansed

apply soap and gently massage area for 1-2 minutes

rinse thoroughly and pat dry

WARNINGS

For external use only

Do not use if

You have no famlly history of hair loss

your hair loss is sudden and/or patchy

you do not know the reason for your hair loss

you are under 18 years of age, Do not use on babies and children

your scalp is red, inflamed, infected, irritated, or painful

you use other medicines on the scalp

Ask a doctor before use if you have heart disease

DOSAGE AND ADMINISTRATION

For external use only.

Stop use and ask a doctor if

chest pain, rapid heartbeat, faintness, or dizziness occurs

sudden, unexplained weight gain occurs

your hands or feet swell

scalp irritation or redness occurs

unwanted facial hair growth occurs

you do not see hair regrowth in 4 months

May be harmful if used when pregnant or breast-feeding.

Keep out of reach of children, lf swallowed, get medical help or contact a Poison Control Center right away.

WHEN USING

do not apply on other parts of the body

avoid contact with the eyes. in case of accidental contact, rinse eyes with large amounts of cool tap water

STOP USE

on broken or irritated scalp

KEEP OUT OF REACH OF CHILDREN

If sxralowed, get medical help or contact a Poison Conirol Cenler ngiht away.

INACTIVE INGREDIENT

Sodium Cocoyl Isethionate

Behentrimonium Methosulfate

Cocoa Butter Glyceryl Esters

Cetyl Alcohol

Shea Butter Oleyl Esters

Stearic Acid

Rice Bran Oil Polyglyceryl-3 Esters

Hydrolyzed Rice Protein

Broccoli Seed Oil Polyglyceryl-4 Esters

Sodium Lactate

Aloe Vera Leaf Extract

Jojoba Oil PEG-8 Esters

Fragrance